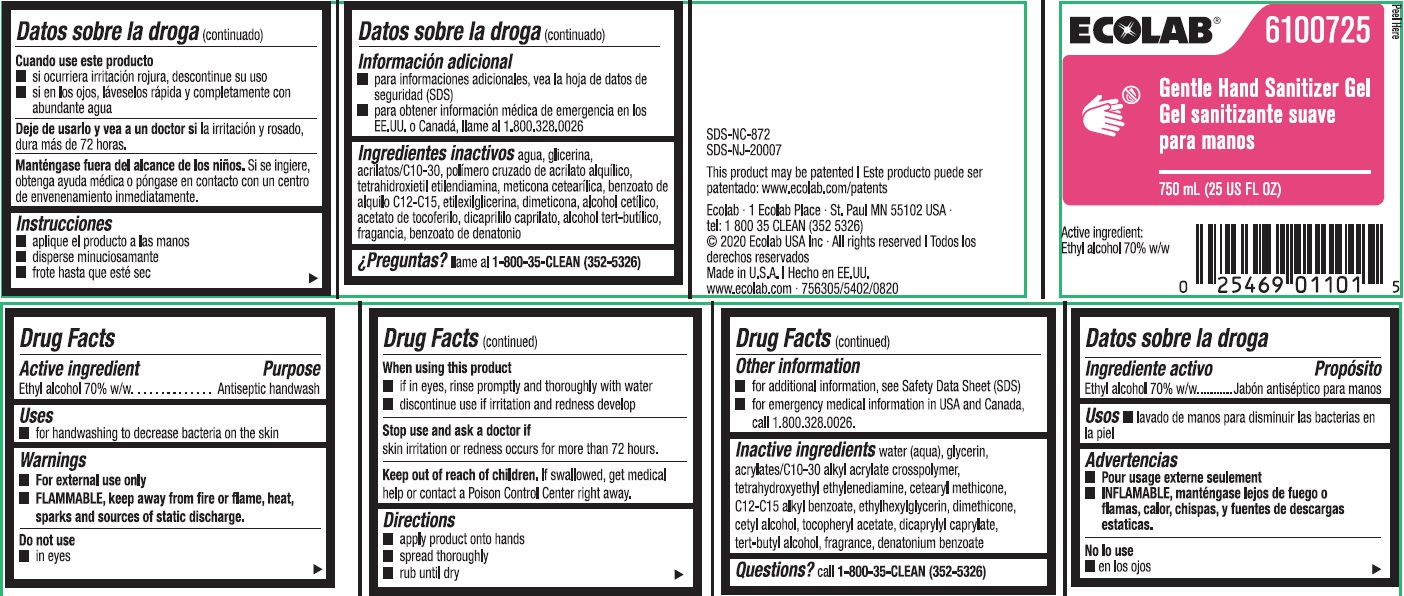 DRUG LABEL: Ecolab
NDC: 47593-509 | Form: LIQUID
Manufacturer: Ecolab Inc.
Category: otc | Type: HUMAN OTC DRUG LABEL
Date: 20251230

ACTIVE INGREDIENTS: ALCOHOL 700 mg/1 mL
INACTIVE INGREDIENTS: WATER; GLYCERIN; CARBOMER INTERPOLYMER TYPE A (ALLYL SUCROSE CROSSLINKED); ETHYLENEDIAMINE TETRAETHANOL; CETEARYL METHICONE (15000 MW); ALKYL (C12-15) BENZOATE; ETHYLHEXYLGLYCERIN; DIMETHICONE; CETYL ALCOHOL; .ALPHA.-TOCOPHEROL ACETATE; DICAPRYLYL CARBONATE; TERT-BUTYL ALCOHOL; DENATONIUM BENZOATE

Drug Facts

Active Ingredient

Ethyl alcohol 70% w/w

Purpose

Antiseptic handwash

Uses

- For handwashing to decrease bacteria on the skin

Warnings

- For external use only
- Flammable, keep away from fire or flame, heat, sparks and sources of static discharge

Do not use

- In eyes

When using this product

- If in eyes, rinse promptly and thoroughly with water
- Discontinue use if irritation and redness develop

Stop use and ask a doctor if

- Skin irritation or redness occurs for more than 72 hours

Keep out of reach of children. If swallowed, get medical help or contact a Poison Control Center right away.

Directions

- Apply product onto hands, spread thoroughly and rub until dry

Other information

- For additional information, see Safety Data Sheet (SDS)
- For emergency medical information in USA and Canada, call 1.800.328.0026

INACTIVE INGREDIENT

Inactive ingredients water (aqua), glycerin, acrylates/C10-30 alkyl acrylate crosspolymer, tetrahydroxyethyl ethylenediamine, cetearyl methicone, C12-C15 alkl benzoate, ethylhexylglycerin, dimethicone, cetyl alcohol, tocopheryl acetate, dicaprylyl caprylate, tert-butyl alcohol, fragrance, denatonium benzoate

Questions? call 1-800-35-CLEAN (352-5326)

Principal Display Panel and Representative Label

ECOLAB®

6100725

Gentle Hand Sanitizer Gel

750 ML (25 US FL OZ)

Active Ingredient: Ethyl alcohol 70% w/w

SDS-NC-872

SDS-NJ-20007

This product may be patented: www.ecolab.com/patents

Ecolab · 1 Ecolab Place · St. Paul MN 55102 USA

© 2020 Ecolab USA Inc · All rights reserved

Made in United States

www.ecolab.com · 756305/5402/0820